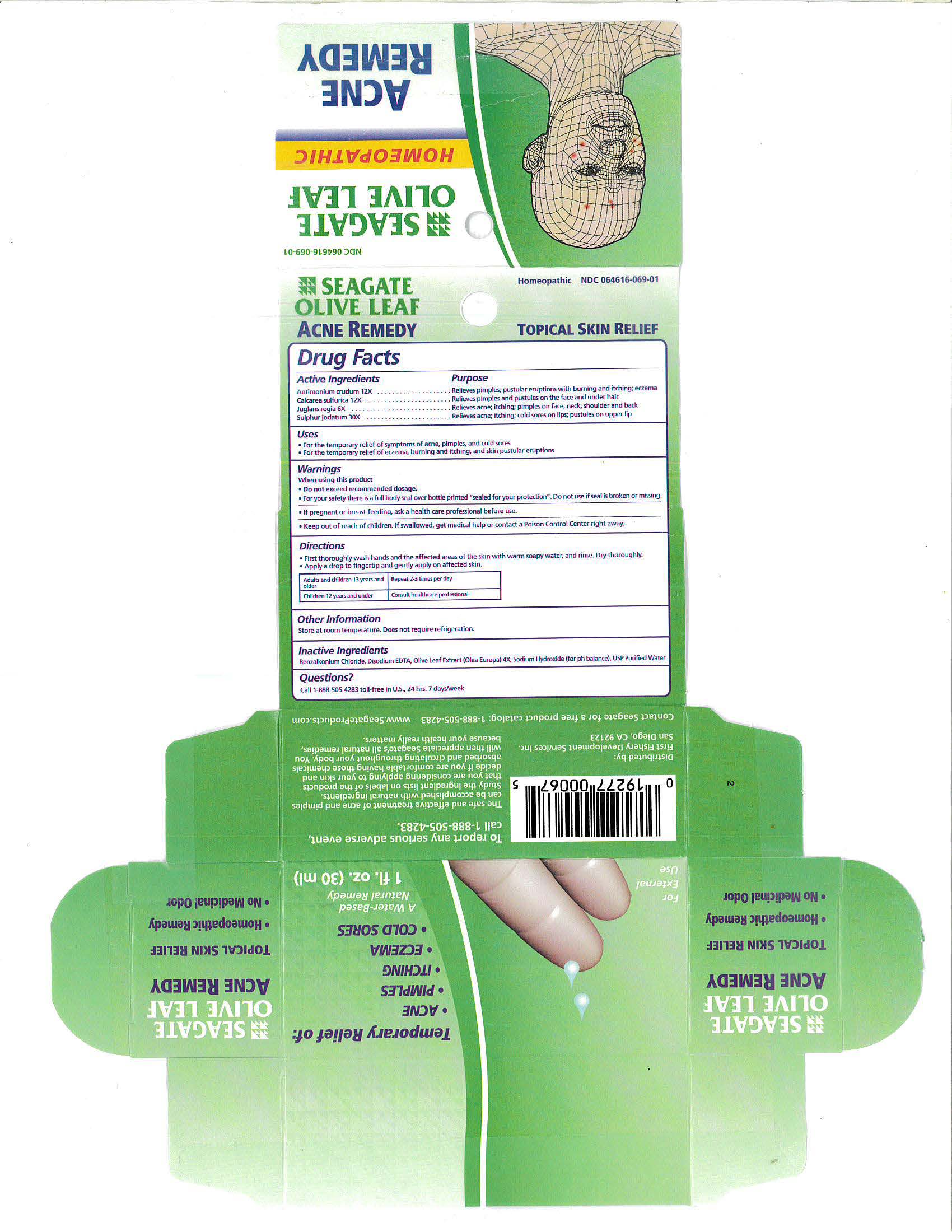 DRUG LABEL: Olive Leaf Acne Remedy
NDC: 64616-069 | Form: LIQUID
Manufacturer: Vitality Works, Inc
Category: homeopathic | Type: HUMAN OTC DRUG LABEL
Date: 20251217

ACTIVE INGREDIENTS: ANTIMONY TRISULFIDE 12 [hp_X]/1 mL; CALCIUM SULFATE ANHYDROUS 12 [hp_X]/1 mL; JUGLANS REGIA FLOWERING TOP 6 [hp_X]/1 mL; SULFUR IODIDE 30 [hp_X]/1 mL
INACTIVE INGREDIENTS: BENZALKONIUM CHLORIDE; WATER; OLEA EUROPAEA LEAF; SODIUM HYDROXIDE; MAGNESIUM DISODIUM EDTA

Olive Leaf Acne Remedy

Olive Leaf Acne Remedy

Antimonium crudum 12X

Calcarea sulfurica 12X

Juglans regia 6X

Sulphur iodatum 30X

Olive Leaf Acne Remedy

USP Purified Water, Xylitol powder, Sodium Chloride, Olive Leaf Extract (Olea europa) 4X, Grapefruit Seed Extract, Sodium Hydroxide (for pH balance)

Olive Leaf Acne Remedy

-Do not apply in or around eyes. This product will sting your eyes. If product should get into your eyes, rinse with warm water.

-As with any drug. If you are pregnanat or nursing a baby, seek the advice of a health care professional before using this product.

-In case of accidental overdose by ingestion, seek profesional assistance or contact a poison control center immediately. All the ingredients are edible. However this product is not designed for internal use.

Olive Leaf Acne Remedy

Keep this and all drugs out of the reach of children. For children under 3 years of age, consult a health care professional.

Olive Leaf Acne Remedy

For the temporary relief of symptoms of acne, pimples, and cold sores.

For the temporary relief of eczema, burning and itching, and skin pustular eruptions.

Olive Leaf Acne Remedy

- First, thoroughly wash hands and the affected areas of the skin with warm soapy water, and rinse. Dry thoroughly.
- Apply a drop to fingertip and gently apply on affected skin.
- Repeat 2-3 times per day.
- For best results, continue using for a least one week after syptoms disappear.
- Reapply if symptoms return.

Olive Leaf Acne Remedy

Antimonium crudum - Relieves pimples; pustular eruptions with burning and itching; eczema

Calcarea sulfurica - Relieves pimples and pustules on the face and under hair

Juglans regia - Relives acne; itching; pimples on face, neck, shoulder and back

Sulphur iodatum - Relieves acne, itching; cold sores on lips; pustules on uppler lip